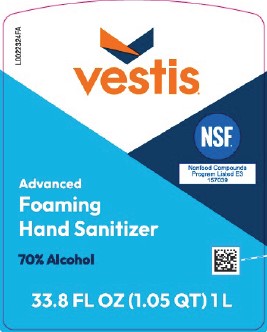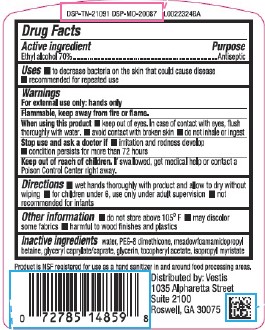 DRUG LABEL: Hand Sanitizer
NDC: 71897-465 | Form: LIQUID
Manufacturer: Veritiv Operating Company
Category: otc | Type: HUMAN OTC DRUG LABEL
Date: 20260216

ACTIVE INGREDIENTS: ALCOHOL 70 mL/100 mL
INACTIVE INGREDIENTS: WATER; PEG-8 DIMETHICONE; GLYCERYL CAPRYLATE/CAPRATE; ISOPROPYL MYRISTATE; .ALPHA.-TOCOPHEROL ACETATE; MEADOWFOAMAMIDOPROPYL BETAINE; GLYCERIN

Vestis 456.001/456AC
70% Alcohol Foaming Hand Sanitizer

Active Ingredient

Ethyl alcohol 70%

Purpose

Antiseptic

Uses

- to decrease bacteria on the skin that could cause disease
- recommended for repeated use

Warnings

For external use only: hands only

Flammable,

keep away from fire or flame.

When using this product

- keep out of eyes. In case of contact with eyes, flush thoroughly with water.
- avoid contact with broken skin
- do not inhale or ingest

Stop use and ask a doctor if

- irritation and redness develop
- condition persists for more than 72 hours

Keep out of reach of children

If swallowed, get medical help or contact a Poison Control Center right away.

Directions

- wet hands thoroughly with product and allow to dry without wiping
- for children under 6, use only under adult supervision
- not recommended for infants

Other information

- do not store above 105⁰ F
- may discolor some fabrics
- harmful to wood finishes and plastics

Inactive ingredients

water, PEG-8 dimethicone, meadowfoamamidopropyl betaine, glyceryl caprylate/caprate, glycerin, tocopheryl acetate, isopropyl myristate

Claim

Product is NSF registered for use as a hand sanitizer in and around food processing areas.

Adverse Reaction

Distributed by: Vestis

1035 Alpharetta Street

Suite 2100

Roswell, GA 30075

DSP-TN-21091 DSP-MO-20087

Principal Display Panel

vestis®

NSF

Nonfood Compounds Program Listed E3 157039

Advanced

Foaming

Hand Sanitizer

70% Alcohol

33.8 FL OZ (1.05 QT) 1 L